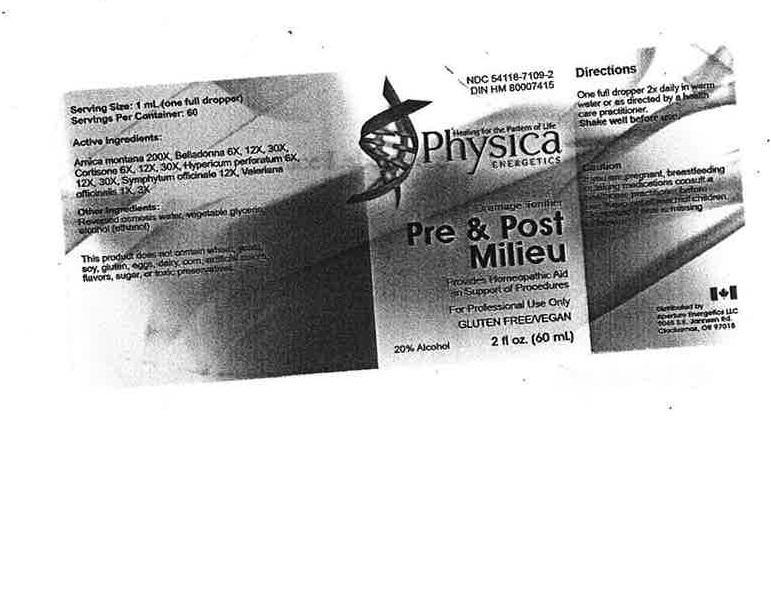 DRUG LABEL: Pre and Post Milieu
NDC: 54118-7109 | Form: SOLUTION/ DROPS
Manufacturer: ABCO Labratories, Inc.
Category: homeopathic | Type: HUMAN OTC DRUG LABEL
Date: 20150825

ACTIVE INGREDIENTS: ARNICA MONTANA 200 [hp_X]/60 mL; BELLADONNA LEAF 6 [hp_X]/60 mL; CORTISONE 6 [hp_X]/60 mL; HYPERICUM PERFORATUM 6 [hp_X]/60 mL; SYMPHYTUM OFFICINALE WHOLE 12 [hp_X]/60 mL; VALERIANA OFFICINALIS WHOLE 1 [hp_X]/60 mL
INACTIVE INGREDIENTS: WATER; GLYCERIN; ALCOHOL

Pre and Post Milieu

WARNINGS

If you are pregnant, breastfeeding or taking medications consult a health care practitioner before use.

Keep out of reach of children.

Do not use if seal is missing or broken.

Keep out of reach of children.

INDICATIONS AND USAGE

Drainage Tonifier

For Professional Use only.

Gluten Free.

PURPOSE

Provides Homeopathic Aid in Support of Procedures.

DOSAGE AND ADMINISTRATION

One full dropper 2x daily in warm water or as directed by a health care practitioner.

INACTIVE INGREDIENT

Reversed osmosis water, vegetable glycerin, alcohol (ethanol).

ACTIVE INGREDIENT

Arnica Montana 200x, Belladonna 6x, Cortisone 6x, Hypericum Perforatum 6x, Symphytum Officinale 12x, Valeriana Officinalis 1x.